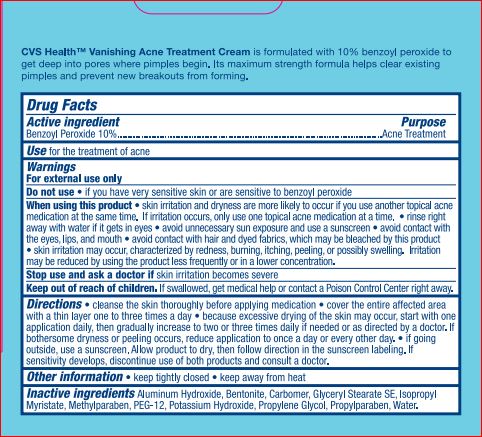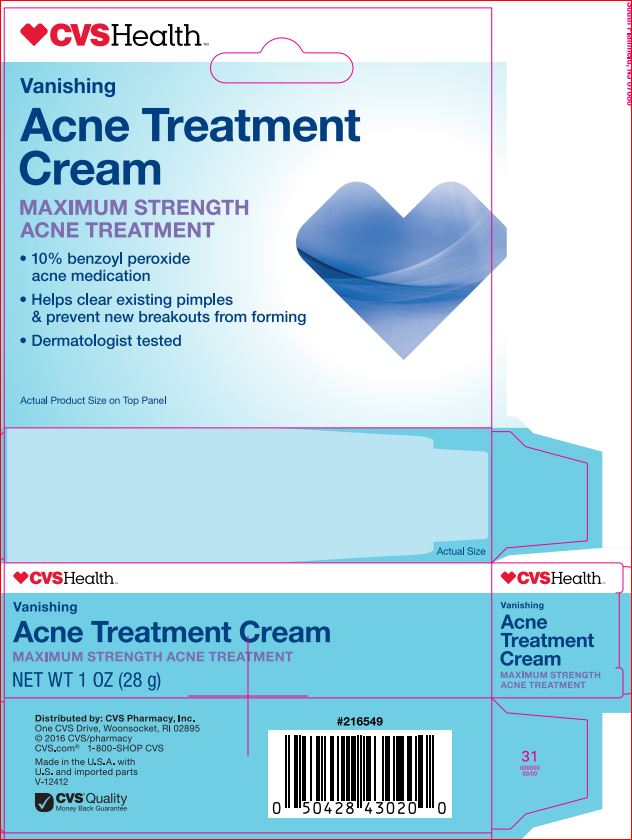 DRUG LABEL: Acne Treatment
NDC: 59779-240 | Form: CREAM
Manufacturer: CVS
Category: otc | Type: HUMAN OTC DRUG LABEL
Date: 20171226

ACTIVE INGREDIENTS: BENZOYL PEROXIDE 10 g/100 g
INACTIVE INGREDIENTS: ALUMINUM HYDROXIDE; BENTONITE; GLYCERYL STEARATE SE; ISOPROPYL MYRISTATE; METHYLPARABEN; POLYETHYLENE GLYCOL 600; POTASSIUM HYDROXIDE; PROPYLENE GLYCOL; PROPYLPARABEN; WATER

Drug Facts

Active ingredient

Benzoyl Peroxide 10%

Purpose

Acne treatment

Uses

For the treatment of acne.

Warnings

For external use only.

Do not use

- if you have very sensitive skin or are sensitive to Benzoyl Peroxide

When using this product

- skin irritation and dryness is more likely to occur if you use another topical acne medication at the same time. If irritation occurs, only use one topical acne medication at a time.
- rinse right away with water if it gets in eyes.
- avoid unnecessary sun exposure and use a sunscreen.
- avoid contact with eyes, lips, and mouth.
- avoid contact with hair and dyed fabrics, which may be bleached by this product.
- skin irritation may occur, characterized by redness, burning, itching, peeling, possibly swelling. Irritation may be reduced by using the product less frequently or in a lower concentration.

Stop and ask a doctor if

- irritation becomes severe

Keep out of reach of children

If swallowed, get medical help or contact a Poison Control Center right away.

Directions

- cleanse the skin thoroughly before applying medication
- cover the entire affected area with a thin layer one to three times a day
- because excessive drying of the skin may occur, start with one application daily, then gradually increase to 2 to 3 times daily if needed or as directed by a doctor. If bothersome dryness or peeling occurs, reduce application to once a day or every other day.
- if going outside, use a sunscreen. Allow product to dry then follow directions in the sunscreen labeling. if sensitivity develops, discontinue use of both products and consult a doctor.

Inactive ingredients

Aluminum hydroxide, Bentonite, Carbomer, Glyceryl Stearate SE, Isopropyl myristate, Methylparaben, PEG-12, Potassium Hydroxide, Propylene Glycol, Propylparaben, Water